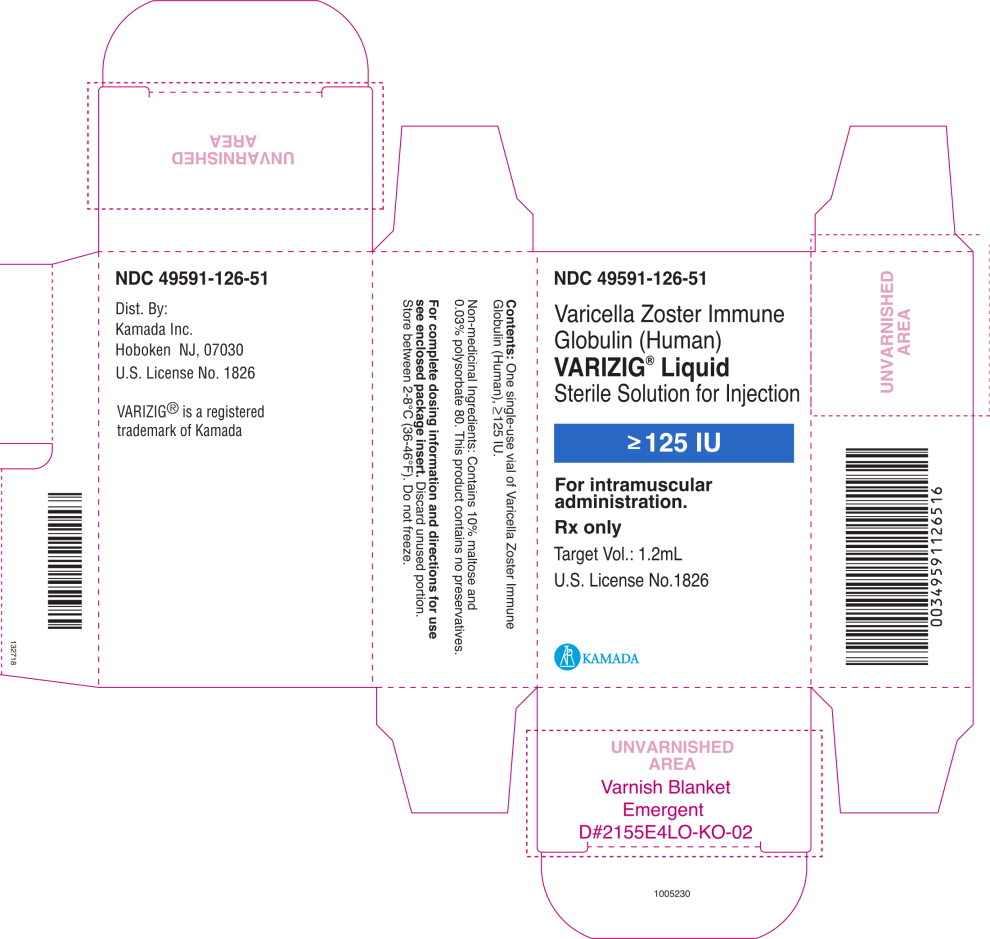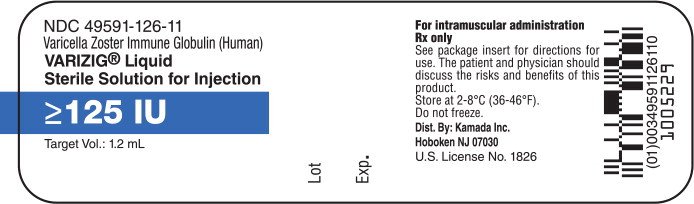 DRUG LABEL: VARIZIG
NDC: 49591-126 | Form: INJECTION, SOLUTION
Manufacturer: Kamada Ltd.
Category: other | Type: PLASMA DERIVATIVE
Date: 20240105

ACTIVE INGREDIENTS: HUMAN VARICELLA-ZOSTER IMMUNE GLOBULIN 125 [iU]/1.2 mL
INACTIVE INGREDIENTS: MALTOSE, UNSPECIFIED FORM; POLYSORBATE 80

HIGHLIGHTS OF PRESCRIBING INFORMATION

These highlights do not include all the information needed to use VARIZIG®safely and effectively. See full prescribing information for VARIZIG.
VARIZIG®[Varicella Zoster Immune Globulin (Human)]
for intramuscular administration only.
Sterile Solution for Injection
Initial U.S. Approval: 2012

1 INDICATIONS AND USAGE

VARIZIG is a Varicella Zoster Immune Globulin (Human) indicated for post-exposure prophylaxis in high risk individuals (1). High risk groups include:

- immunocompromised children and adults,
- newborns of mothers with varicella shortly before or after delivery,
- premature infants,
- infants less than one year of age,
- adults without evidence of immunity,
- pregnant women.

VARIZIG administration is intended to reduce the severity of varicella.

2 DOSAGE AND ADMINISTRATION

Intramuscular use only.

Dosing of VARIZIG is based on body weight. Administer a single dose of VARIZIG intramuscularly as recommended in the following table (2.1):

Weight of Patient (kg) | Dose (international units) | Number of Vials
≤2.0 | 62.5 | 0.5
2.1–10.0 | 125 | 1
10.1–20.0 | 250 | 2
20.1–30.0 | 375 | 3
30.1–40.0 | 500 | 4
>40.1 | 625 | 5
≤: less than or equal to
>: greater than

Discard any partial vials.

The intramuscular dose should be divided and administered in two sites, dependent on patient size. Do not exceed 3 mL per injection site (2.2).

3 DOSAGE FORMS AND STRENGTHS

VARIZIG is supplied as a sterile solution for intramuscular injection and is available in a single-use vial of 125 international units in 1.2 mL (3).

4 CONTRAINDICATIONS

- History of anaphylactic or severe systemic reactions to human immune globulins (4).
- IgA-deficient patients with antibodies against IgA and a history of hypersensitivity (4).

5 WARNINGS AND PRECAUTIONS

- Thrombotic events (5.1)
- Coagulation disorders (5.2)
- Hypersensitivity (5.3)
- Transmissible infectious agents (5.4)

6 ADVERSE REACTIONS

Most common adverse reactions from clinical trials are pain at the injection site (3%) and headache (2%) (6).

To report SUSPECTED ADVERSE REACTIONS, contact Kamada. at 1-866-916-0077 or FDA at 1-800-FDA-1088 or www.fda.gov/medwatch.

7 DRUG INTERACTIONS

- Efficacy of live attenuated virus vaccines may be impaired by immune globulin administration; revaccination may be necessary (7).

8 USE IN SPECIFIC POPULATIONS

- Pregnancy: Use only if clearly needed (8.1)
- Lactation: Caution should be exercised (8.2)

FULL PRESCRIBING INFORMATION

1 INDICATIONS AND USAGE

VARIZIG®[Varicella Zoster Immune Globulin (Human)] is indicated for post-exposure prophylaxis of varicella in high risk individuals. High risk groups include:

- immunocompromised children and adults,
- newborns of mothers with varicella shortly before or after delivery,
- premature infants,
- neonates and infants less than one year of age,
- adults without evidence of immunity,
- pregnant women.

VARIZIG administration is intended to reduce the severity of varicella. Administer VARIZIG as soon as possible following varicella zoster virus (VZV) exposure, ideally within 96 hours for greatest effectiveness.

- There is no convincing evidence that VARIZIG reduces the incidence of chickenpox infection after exposure to VZV.
- There is no convincing evidence that established infections with VZV can be modified by VARIZIG administration.
- There is no indication for the prophylactic use of VARIZIG in immunodeficient children or adults when there is a past history of varicella, unless the patient is undergoing bone marrow transplantation.

2 DOSAGE AND ADMINISTRATION

For intramuscular use only.

2.1 Preparation and Handling

Each vial of VARIZIG contains a minimum potency of 125 international units in 1.2 mL.

Bring VARIZIG to room temperature prior to use.

Inspect VARIZIG for particulate matter and discoloration prior to administration. Do not use if the solution is cloudy or contains particulates.

VARIZIG is for single use only. Discard any unused portion.

Dosing of VARIZIG is based on body weight. Administer a single dose of VARIZIG intramuscularly as recommended in Table 1.

The minimum dose is 62.5 international units for small infants under two kilograms body weight; the maximum dose of 625 international units should be administered for all patients greater than 40 kilograms in weight.

Table 1 VARIZIG Dose and Volume of Administration
Weight of Patient |  | VARIZIG Dose |  | Volume to Administer* (milliliters)
Kilograms | Pounds | international units | Number of Vials | Volume to Administer* (milliliters)
≤2.0 | ≤4.4 | 62.5 | 0.5 | 0.6
2.1–10.0 | 4.5–22.0 | 125 | 1 | 1.2
10.1–20.0 | 22.1–44.0 | 250 | 2 | 2.4
20.1–30.0 | 44.1–66.0 | 375 | 3 | 3.6
30.1–40.0 | 66.1–88.0 | 500 | 4 | 4.8
≥40.1 | ≥88.1 | 625 | 5 | 6.0
*Extractable volumes are confirmed using a 21 gauge needle as per USP General Chapters <1> Injections.
≤: less than or equal to
≥: greater than or equal to

Consider a second full dose of VARIZIG for high risk patients who have additional exposures to varicella greater than three weeks after initial VARIZIG administration.

2.2 Administration

For intramuscular use only.

Divide the intramuscular dose and administer in two or more injection sites, depending on patient size. Do not exceed 3 milliliters per injection site.

Inject into the deltoid muscle or the anterolateral aspects of the upper thigh. Due to the risk of sciatic nerve injury, do not use the gluteal region as a routine injection site. If the gluteal region is used, only use the upper, outer quadrant.

To prevent the transmission of infectious agents from one person to another, use a new disposable sterile syringe and needle for each individual patient.

3 DOSAGE FORMS AND STRENGTHS

VARIZIG is supplied as a sterile solution for intramuscular injection and is available in a single-use vial of 125 international units. Each 125 international units vial of VARIZIG contains less than 180 milligrams of total protein, mostly human immune globulin G (IgG). VARIZIG contains no preservative and is intended for single use only. VARIZIG does not contain mercury.

4 CONTRAINDICATIONS

- Individuals known to have anaphylactic or severe systemic (hypersensitivity) reactions to human immune globulin preparations should not receive VARIZIG.
- IgA-deficient patients with antibodies against IgA and a history of hypersensitivity may have an anaphylactoid reaction.
- VARIZIG contains less than 40 micrograms per milliliter of IgA.

5 WARNINGS AND PRECAUTIONS

5.1 Thrombotic Events

Thrombotic events may occur during or following treatment with immune globulin products (1, 2, 3). Patients at risk include those with a history of atherosclerosis, multiple cardiovascular risk factors, advanced age, impaired cardiac output, coagulation disorders, prolonged periods of immobilization, and/or known/suspected hyperviscosity. Consider baseline assessment of blood viscosity in patients at risk for hyperviscosity including those with cryoglobulins, fasting chylomicronemia/markedly high triacylglycerols (triglycerides), or monoclonal gammopathies.

5.2 Coagulation Disorders

Administer VARIZIG intramuscularly only. In patients who have severe thrombocytopenia or any coagulation disorder that would contraindicate intramuscular injections, only administer VARIZIG if the expected benefits outweigh the potential risks.

5.3 Hypersensitivity

Severe hypersensitivity reactions may occur following VARIZIG administration. Administer VARIZIG in a setting with appropriate equipment, medication and personnel trained in the management of hypersensitivity, anaphylaxis and shock. In the case of hypersensitivity, discontinue administration of VARIZIG immediately and provide appropriate treatment.

VARIZIG contains trace amounts of IgA (less than 40 micrograms per milliliter). Patients with known antibodies to IgA have a greater risk of severe hypersensitivity and anaphylactic reactions. VARIZIG is contraindicated in IgA deficient patients with antibodies against IgA and history of hypersensitivity reactions [see 4 CONTRAINDICATIONS].

5.4 Transmissible Infectious Agents

Because VARIZIG is made from human plasma, it may carry a risk of transmitting infectious agents, e.g., viruses, the variant Creutzfeldt-Jakob disease (vCJD) agent and, theoretically, the Creutzfeldt-Jakob disease (CJD) agent. The plasma donors are screened for the presence of certain infectious agents and the manufacturing process for VARIZIG includes measures to inactivate and remove certain viruses [see 11DESCRIPTION ]. Despite these measures, products derived from human plasma can still potentially transmit diseases. No cases of transmission of viral diseases, vCJD or CJD have been associated with the use of VARIZIG.

Report all infections thought by a physician to have been transmitted by VARIZIG to Kamada at 1-866-916-0077. Discuss the risks and benefits of this product with the patient before administering it to the patient [see 17PATIENT COUNSELING INFORMATION ].

6 ADVERSE REACTIONS

The most serious adverse drug reactions observed in clinical trials for all subjects and patients (n=601) include pyrexia, nausea, and vomiting.

The most common adverse drug reactions (reported by greater than or equal to 1% of subjects) observed in clinical trials for all subjects and patients (n=601) are the following:

- injection site pain (3%),
- headache (2%),
- rash (including terms pruritus, rash, rash erythematous, rash vesicular and urticaria) (1%),
- fatigue (1%),
- chills (1%),
- nausea (1%).

All other adverse drug reactions occurred in less than 1%.

6.1 Clinical Trial Experience

Because clinical trials are conducted under widely varying conditions, adverse reaction rates observed in the clinical trials of a drug cannot be directly compared to rates in the clinical trials of another drug and may not reflect the rates observed in practice.

Six hundred and one (n=601) high risk individuals received VARIZIG intramuscularly in two clinical trials which included pregnant women, infants and immunocompromised pediatric and adult patients. The highest incidence of adverse reactions occurred in pregnant women (n=166), including injection site pain (7%), rash (including terms pruritus, rash, rash erythematous, and rash vesicular) (4%), headache (3%), and fatigue (2%). All other adverse reactions occurred in 1% or less of clinical trial subjects within each high risk group. A single incidence of serum sickness (approximately one in 600 patients treated with VARIZIG) was observed in an immunocompromised adolescent patient.

There were eight reported adverse events associated with the coagulation system including, deep vein thrombosis (n=1), disseminated intravascular coagulation (n=1) , intracranial hemorrhage (n=2), coagulopathy (n=2), intraventricular hemorrhage (n=1), and pulmonary hemorrhage (n=1) in 621 subjects in the open-label, Expanded Access Protocol (EAP); the study was not designed to differentiate between adverse events attributed to the underlying medical condition and adverse reactions to VARIZIG.

7 DRUG INTERACTIONS

The passive transfer of antibodies with immune globulin administration may impair the efficacy of live attenuated virus vaccines such as measles, rubella, mumps and varicella. Defer vaccination with live virus vaccines until approximately three months after VARIZIG administration. Inform the immunizing physician of recent therapy with VARIZIG so that appropriate measures can be taken [see 17PATIENT COUNSELING INFORMATION ].

8 USE IN SPECIFIC POPULATIONS

8.1 Pregnancy

Animal reproduction studies have not been conducted with VARIZIG. It also is not known whether VARIZIG can cause fetal harm when administered to a pregnant woman or can affect reproduction capacity. VARIZIG should be given to a pregnant woman only if clearly needed.

The safety and effectiveness of VARIZIG have been evaluated for post-exposure prophylaxis in clinical trials in 166 pregnant women [see 6 ADVERSE REACTIONSand 14 CLINICAL STUDIES].

8.2 Lactation

It is not known whether VARIZIG is excreted in human milk. Because many drugs are excreted in human milk, caution should be exercised when VARIZIG is administered to a nursing mother.

8.4 Pediatric Use

The dosing recommendations in the treatment of pediatric patients are by body weight [see 2 DOSAGE AND ADMINISTRATION].

The safety and effectiveness of VARIZIG have been evaluated for post-exposure prophylaxis in the VARIZIG expanded access clinical trial in 374 pediatric patients, including immunocompromised pediatric patients:

- 94 preterm newborns and infants,
- 53 term newborns,
- 45 infants and toddlers,
- 176 children and,
- 43 adolescents.

In the EAP, follow up data were available for 110 VARIZIG treatments in infants (including newborns, pre-term infants, and infants less than 1 year old). Three severe infections were reported, all three with pox count greater than 100, one of which also had pneumonia and another one also developed probable varicella encephalitis.

8.5 Geriatric Use

Clinical studies of VARIZIG administered intramuscularly for post-exposure prophylaxis did not include sufficient numbers of geriatric subjects (aged 65 and over) to determine whether they respond differently from younger subjects.

Use caution when administering VARIZIG to patients aged 65 and over who are judged to be at increased risk of thrombotic events [see 5 WARNINGS AND PRECAUTIONS]. Do not exceed recommended doses and administer VARIZIG intramuscularly only.

8.6 Immunocompromised Patients

In the EAP, both adult (n=37) and pediatric immunocompromised subjects (n=235) were treated. Twelve immunocompromised subjects developed clinical varicella and none developed varicella pneumonitis; however at least five are reported to have received concomitant acyclovir and due to incomplete reporting, it is not known if others also received acyclovir.

10 OVERDOSAGE

Manifestations of an overdose of VARIZIG administered intramuscularly are expected to be pain and tenderness at the injection site.

11 DESCRIPTION

VARIZIG [Varicella Zoster Immune Globulin (Human)] is a solvent/detergent-treated sterile liquid preparation of purified human immune globulin G (IgG) containing antibodies to varicella zoster virus (anti-VZV). VZV is the causative agent of chickenpox. VARIZIG is prepared from plasma donated by healthy, screened donors with high titers of antibodies to VZV, which is purified by an anion-exchange column chromatography manufacturing method. This donor selection process includes donors with high anti-VZV titers due to recent natural infection by VZV, or due to recurrent zoster infection (shingles).

VARIZIG is intended for single use and should be administered intramuscularly [see 2 DOSAGE AND ADMINISTRATION].

The product potency is expressed in international units by comparison to the World Health Organization (WHO) international reference preparation for anti-VZV immune globulin. Each vial contains 125 international units of anti-VZV. VARIZIG is formulated with 10% maltose and 0.03% polysorbate 80. VARIZIG has a pH of 5.0 – 6.5 and contains no preservative.

The presence of anti-Protein S antibodies has been reported to arise transiently in patients after VZV infection (4). Low levels of anti-Protein S antibodies have been reported in VARIZIG.

The source plasma used in the manufacture of this product was tested by FDA licensed nucleic acid testing (NAT) for human immunodeficiency virus-1 (HIV-1), hepatitis B virus (HBV) and hepatitis C virus (HCV) and found to be negative. Plasma also was tested by in-process NAT for hepatitis A virus (HAV) and parvovirus B19 (B19) via minipool testing; the limit for B19 in the manufacturing pool is set not to exceed 10^4international units of B19 DNA per milliliter.

The manufacturing process contains two steps implemented specifically for virus clearance. The solvent/detergent step (using tri-n-butyl phosphate and Triton®X-100) is effective in the inactivation of enveloped viruses, such as HBV, HCV and HIV-1. Virus filtration, using a Planova®20N virus filter, is effective for the removal of viruses based on their size, including some non-enveloped viruses. These two viral clearance steps are designed to increase product safety by reducing the risk of transmission of enveloped and non-enveloped viruses. In addition to these two specific steps, the process step of anion-exchange chromatography was identified as contributing to the overall viral clearance capacity for small non-enveloped viruses.

The inactivation and reduction of known enveloped and non-enveloped model viruses were validated in laboratory studies as summarized in Table 2. The viruses employed for spiking studies were selected to represent those viruses that are potential contaminants in the product, and to represent a wide range of physiochemical properties in order to challenge the manufacturing process's ability for viral clearance in general.

Table 2 Virus Reduction Values (Log10) Obtained through Validation Studies
 | Enveloped |  |  | Non-Enveloped
Genome | RNA |  | DNA | RNA |  |  | DNA
Virus | HIV-1 | BVDV | PRV | HAV |  | EMC | MMV | PPV
Family | retro | flavi | herpes | picorna |  |  | parvo
Size (nm) | 80–100 | 50–70 | 120–200 | 25–30 |  | 30 | 20–25 | 18–24
Anion Exchange Chromatography (partitioning) | Not evaluated |  |  | 2.3 |  | n.e. | 3.4 | n.e.
20N Filtration (size exclusion) | ≥4.7 | ≥3.5 | ≥5.6* | n.e. |  | 4.8 | n.e. | 4.1
Solvent/Detergent (inactivation) | ≥4.7 | ≥7.3 | ≥5.5 | Not evaluated
Total Reduction (log10) | ≥9.4 | ≥10.8 | ≥11.1 | 2.3 | 4.8 |  | 3.4 | 4.1
*The PRV was retained by the 0.1 μm pre-filter during the virus validation. Since manufacturing employs a 0.1 μm pre-filter before the 20N filter, the claim of greater than or equal to 5.6 reduction is considered applicable.
Abbreviations:
≥: greater than or equal to
HIV-1: human immunodeficiency virus-1; relevant virus for human immunodeficiency virus-1 and model for HIV-2
BVDV: bovine viral diarrhea virus; model virus for hepatitis C virus (HCV) and West Nile virus (WNV)
PRV: pseudorabies virus; model for large enveloped DNA viruses, including herpes
HAV: human hepatitis A virus; relevant virus for HAV and model for small non-enveloped viruses in general
EMC: encephalomyocarditis virus; model for HAV and for small non-enveloped viruses in general
MMV: murine minute virus; model for human parvovirus B19 and for small non-enveloped viruses in general
n.e.: not evaluated

12 CLINICAL PHARMACOLOGY

12.1 Mechanism of Action

VARIZIG provides passive immunization for non-immune individuals exposed to VZV, reducing the severity of varicella infections (5).

12.3 Pharmacokinetics

In a comparative pharmacokinetic clinical trial, 35 volunteers were administered an intramuscular dose of 12.5 international units/kg of VARIZIG (n=18) or the comparator product VZIG (n=17). The dose of 12.5 international units/kg of VZIG or VARIZIG given to the subjects was based on the assumption that the potency was similar for both products. For the bioequivalence analysis, a potency correction factor was applied (concentrations of VARIZIG were multiplied by 2.3) to account for higher measured potency of the comparator product. The mean peak concentration (Cmax) of varicella antibodies occurred within five days of administration for both products (Table 3). In the trial, baseline levels of anti-VZV antibodies ranged from 0 to 720 milli-international units/mL, therefore baseline levels were taken into account for pharmacokinetic calculations, to better represent the indicated population. After potency correction, baseline correction, and exclusion of subjects with baseline values of anti-VZV antibody levels of greater than 200milli-international /mL, the two products were pharmacokinetically comparable.

Table 3 Pharmacokinetic Comparison of VARIZIG and VZIG
PK Parameters* | VARIZIG | VZIG | Ratio 90% Confidence Interval
AUC0-28 (mIUxDay/mL) | 2472 ± 970 | 2347 ± 535 | 84.1–124.6
AUC0-84 (mIUxDay/mL) | 4087 ± 1620 | 3916 ± 964 | 82.0–125.6
Cmax (mIU/mL) | 136 ± 66 | 138 ± 22 | 76.5–112.8
Tmax (Days) | 4.5 ± 2.8 | 3.3 ± 1.5 | Not applicable
t1/2** (Days) | 26.2 ± 4.6 | 23.1 ± 8.6 | Not applicable
CL/F (mL/Day) | 0.204 ± 0.045 | 0.199 ± 0.087 | Not applicable
* Potency and subgroup analysis were implemented for pharmacokinetic calculations. Study subjects with elevated baseline anti-VZV levels (greater than or equal to 200 milli-international units/mL) from both treatment groups were excluded from pharmacokinetic calculations.
** The half-life is expected to vary from patient to patient.
mIU: milli-international units
±: plus or minus

14 CLINICAL STUDIES

14.1 Pregnant Women Exposed to Varicella Zoster Virus

A randomized, open-label, multicenter, active controlled clinical trial was conducted in 60 pregnant women without immunity to VZV as confirmed by a latex agglutination test. Patients were stratified on the basis of time from first exposure to varicella as follows:

- one to four days post-exposure and,
- five to 14 days post-exposure.

The women were randomized into one of three study arms as follows:

- a single intravenous dose of 125 international units/10 kg body weight to a maximum dose of 625 international units of VARIZIG,
- a single intramuscular dose of 125 international units/10 kg body weight to a maximum dose of 625 international units of VARIZIG or,
- a single intramuscular dose of 125 international units/10 kg body weight to a maximum dose of 625 international units of VZIG (licensed comparator product).

Patients were followed for 42 days.

Incidence of clinical varicella was similar across all treatment groups with an overall incidence of 33%; however, in the subset of 28 subjects with more than 24 hours exposure to varicella, the incidence of clinical varicella in the combined treatment groups was 64%.

Mean weighted constitutional illness scores (CIS) (6) were similar across all groups and none of the subjects had serious complications of varicella. The small number of subjects in each treatment stratum and the lack of agreed upon pre-specified hypothesis testing precluded formal statistical comparisons between groups.

14.2 High Risk Patients Exposed to Varicella Zoster Virus

An open-label, Expanded Access Protocol (EAP) conducted in the United States of America was designed to provide VARIZIG to high risk individuals who were exposed to varicella zoster virus (VZV). Although the study was not designed to evaluate efficacy, the objective of the study was to further assess and confirm the safety and efficacy of intramuscular injection of VARIZIG in the prevention or reduction of severity of complications from varicella infections in the indicated high risk populations. Initially, enrollment was limited to allow treatment with VARIZIG only within 96 hours of exposure, but the protocol was amended to expand the treatment window to 10 days post-exposure.

The incidence of clinical varicella (chickenpox lesions), was compared to predefined historical reference rates. The incidence of severe varicella complications, including pneumonia, encephalitis, severe varicella with pox counts greater than 100 pox, mortality and all complications was also evaluated. The overall incidence of clinical varicella was evaluated in an interim analysis, where 10% (31/311) of high risk individuals exposed to VZV and treated with VARIZIG for all combined populations, for whom complete or partial efficacy data was available. Clinical varicella was observed in 8.4% (13/154) of immunocompromised pediatric and adult patients, in 6.8 % (5/74) of pregnant women, in 14.8% (12/81) of infants and one healthy adult (Table 4). Clinical varicella was more common after prolonged VZV exposure. The final report confirmed the efficacy results in the interim analysis (Table 5). In addition, a comparison of the incidence of varicella based on treatment window revealed that treatment between 5 and 10 days post-exposure was no different from treatment within 96 hours.

Table 4 Comparison of Varicella Incidence in Subjects Treated with VARIZIG to Historical Incidence of Varicella in Untreated Individuals – Interim analysis
High Risk Population | Historical Incidence of Varicella in Untreated Individuals | n^1 | Incidence of Varicella in VARIZIG-treated Subjects | 95% Confidence Interval | p-value^2
Pregnant Women | 70% | 74 | 6.8% (n=5) | (2.2–15.1%) | <0.0001*
Immunocompromised patients | 88% | 154 | 8.4% (n=13) | (4.6–14.0%) | <0.0001*
Infants | 50% | 81 | 14.8% (n=12) | (7.9–24.5%) | <0.0001*
^1n = number of VARIZIG doses for post-exposure prophylaxis of varicella in efficacy population.
^2One sample two-sided exact binomial test.
* Statistically significant (α=0.05)
<: less than

Table 5 Updated Summary of Incidence of Varicella in Subjects Treated with VARIZIG – Final Report
High Risk Population | All VARIZIG Treated Subjects
High Risk Population | n^1 | Incidence of Varicella in VARIZIG-treated Subjects | 95% Confidence Interval
Pregnant Women | 137 | 7.3% (n=10) | (3.6% - 13.0%)
Immunocompromised patients | 269 | 4.5% (n=12) | (2.3% - 7.7%)
Infants including newborns, pre-term infants and infants less than 1 year | 105 | 11.4% (n=12) | (6.1% - 19.1%)
^1n = number of VARIZIG doses for post-exposure prophylaxis of varicella in efficacy population

15 REFERENCES

1. Dalakas MC. High-dose intravenous immunoglobulin and serum viscosity: risk of precipitating thromboembolic events. Neurology. 1994; 44:223-6.
2. Woodruff RK, Grigg AP, Firkin FC, Smith IL. Fatal thrombotic events during treatment of autoimmune thrombocytopenia with intravenous immunoglobulin in elderly patients. Lancet. 1986; 2:217-8.
3. Wolberg AS, Kon RH, Monroe DM, Hoffman M. Coagulation factor XI is a contaminant in intravenous immunoglobulin preparations. Am J Hematol. 2000; 65:30-4.
4. Josephson C, Nuss R, Jacobson L, Hacker MR, Murphy J, Weinberg A et al. The Varicella-Autoantibody Syndrome. Pediatr Res. 2001; 50:345-52.
5. CDC. Prevention of varicella. Recommendations of the Advisory Committee on Immunization Practices (ACIP). MMWR. 2007; 56(No. RR-4):1-30.
6. Koren G, Money D, Boucher M, Aoki F, Petric M, Innocencion G et al. Serum concentrations, efficacy, and safety of a new, intravenously administered varicella zoster immune globulin in pregnant women. J Clin Pharmacol. 2002; 42(3):267-74.

16 HOW SUPPLIED/STORAGE AND HANDLING

16.1 How Supplied

NDC 49591-126-51: VARIZIG [Varicella Zoster Immune Globulin (Human)] is supplied as a sterile liquid approximately 125 international units of anti-VZV in a glass tubing vial and a package insert.

16.2 Storage and Handling

Store VARIZIG at 2 to 8°C (36 to 46°F). Do not freeze. Do not use after expiration date.

17 PATIENT COUNSELING INFORMATION

Inform patients of the following:

- VARIZIG is intended to reduce the severity of chickenpox infections. Please see your doctor if you develop the signs and symptoms of varicella.
- VARIZIG is prepared from human plasma and therefore, may contain infectious agents such as viruses that can cause disease.
- The risk that products derived from human plasma will transmit an infectious agent has been reduced by screening plasma donors for prior exposure to certain viruses, by testing for the presence of certain current virus infections, and by inactivating and/or removing certain viruses during manufacturing.
- Despite these measures, products derived from human plasma can still potentially transmit disease.
- There is also the possibility that unknown infectious agents may be present in such products.

Tell patients that persons known to have severe, potentially life-threatening reactions to human immune globulin products should not receive VARIZIG or any other immune globulin products unless the risk has been justified.

Tell patients that persons who are deficient in IgA may have the potential for developing anti-IgA antibodies and have severe potentially life threatening allergic reactions.

- In the case of allergic or anaphylactic reaction, administration should be stopped immediately.
- In the case of shock, the current medical standards for treatment of shock should be administered.

Inform patients that administration of immune globulin may interfere with the response to live virus vaccines (e.g. measles, mumps, rubella and varicella), and instruct them to notify their immunizing physician of recent therapy with VARIZIG.

VARIZIG®[Varicella Zoster Immune Globulin (Human)] Sterile Solution for Injection and any and all Kamada brand, product, service and feature names, logos, slogans are trademarks or registered trademarks of Kamada. All rights reserved.

PLANOVA®is a registered trademark of Asahi Kasei Medical Co., Ltd, TRITON®is a registered trademark of Union Carbide Corporation.

Distributed by:
Kamada Inc.
Hoboken, NJ 07030
U.S. License No. 1826

Principal Display Panel – 1.2 mL Carton Label

NDC 49591-126-51

Varicella Zoster Immune
Globulin (Human)
VARIZIG®Liquid
Sterile Solution for Injection

≥ 125 IU

For intramuscular
administration.

Rx only

Target Vol.: 1.2mL

U.S. License No.1826

KAMADA

Principal Display Panel – 1.2 mL Vial Label

NDC 49591-126-11

Varicella Zoster Immune Globulin (Human)
VARIZIG®Liquid
Sterile Solution for Injection

≥ 125 IU

Target Vol.: 1.2mL